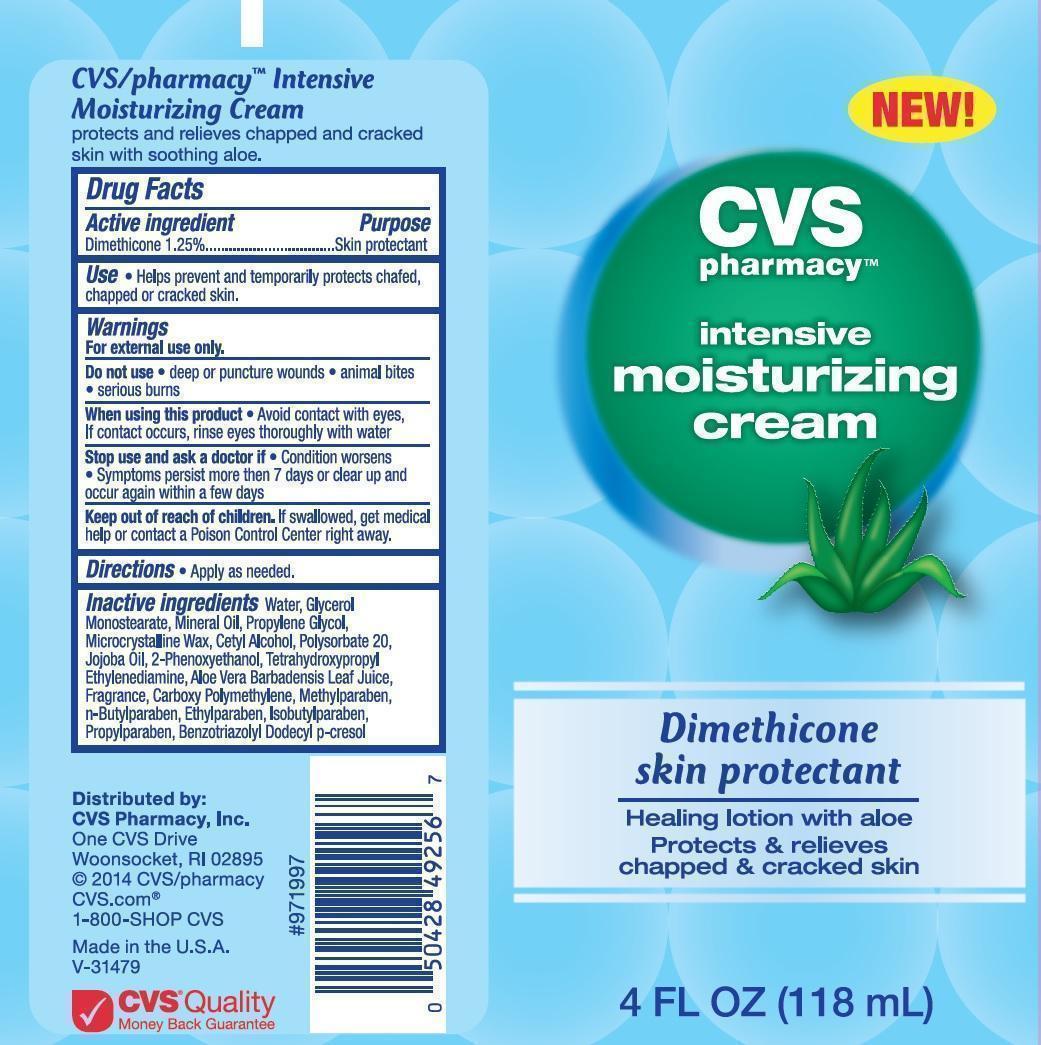 DRUG LABEL: CVS Pharmacy
NDC: 59779-989 | Form: CREAM
Manufacturer: CVS Pharmacy
Category: otc | Type: HUMAN OTC DRUG LABEL
Date: 20140520

ACTIVE INGREDIENTS: DIMETHICONE 12.5 mg/1 mL
INACTIVE INGREDIENTS: WATER; GLYCERYL MONOSTEARATE; MINERAL OIL; PROPYLENE GLYCOL; MICROCRYSTALLINE WAX; CETYL ALCOHOL; POLYSORBATE 20; JOJOBA OIL; PHENOXYETHANOL; EDETOL; ALOE VERA LEAF; CARBOMER COPOLYMER TYPE B (ALLYL PENTAERYTHRITOL CROSSLINKED); METHYLPARABEN; BUTYLPARABEN; ETHYLPARABEN; ISOBUTYLPARABEN; PROPYLPARABEN; BENZOTRIAZOLYL DODECYL P-CRESOL

CVS Pharmacy Intensive Moisturizing Cream - Drug Facts

Active ingredient

Dimethicone 1.25%

Purpose

Skin protectant

Use

- Helps prevent and temporarily protects chafed, chapped or cracked skin.

Warnings

For external use only.

Do not use

- deep or puncture wounds
- animal bites
- serious burns

When using this product

- Avoid contact with eyes, If contact occurs, rinse thoroughly with water

Stop use and ask a doctor if

- Condition worsens
- Symptoms persist more than 7 days or clear up and occur again within a few days

Keep out of reach of children.

If swallowed, get medical help or contact a Poison Control Center right away.

Directions

- Apply as needed.

Inactive ingredients

Water, Glycerol Monostearate, Mineral Oil, Propylene Glycol, Microcrystalline Wax, Cetyl Alcohol, Polysorbate 20, Jojoba Oil, 2-Phenoxyethanol, Tetrahydroxypropyl Ethylenediamine, Aloe Vera Barbadensis Leaf Juice, Fragrance, Carboxy Polymethylene, Methylparaben, n-Butylparaben, Ethylparaben, Isobutylparaben, Propylparaben, Benzotriazolyl Dodecyl p-cresol

Distributed by: CVS Pharmacy, Inc.

One CVS Drive

Woonsocket, RI 02895

© 2014 CVS/pharmacy

CVS.com®

1-800-SHOP CVS

Made in the U.S.A.

Image of CVS Pharmacy Intensive Moisturizing Lotion Label Dimethicone skin protectant 4 FL OZ (118 mL)

CVSIntensiveMoisturizingCream4ozLabel.jpg